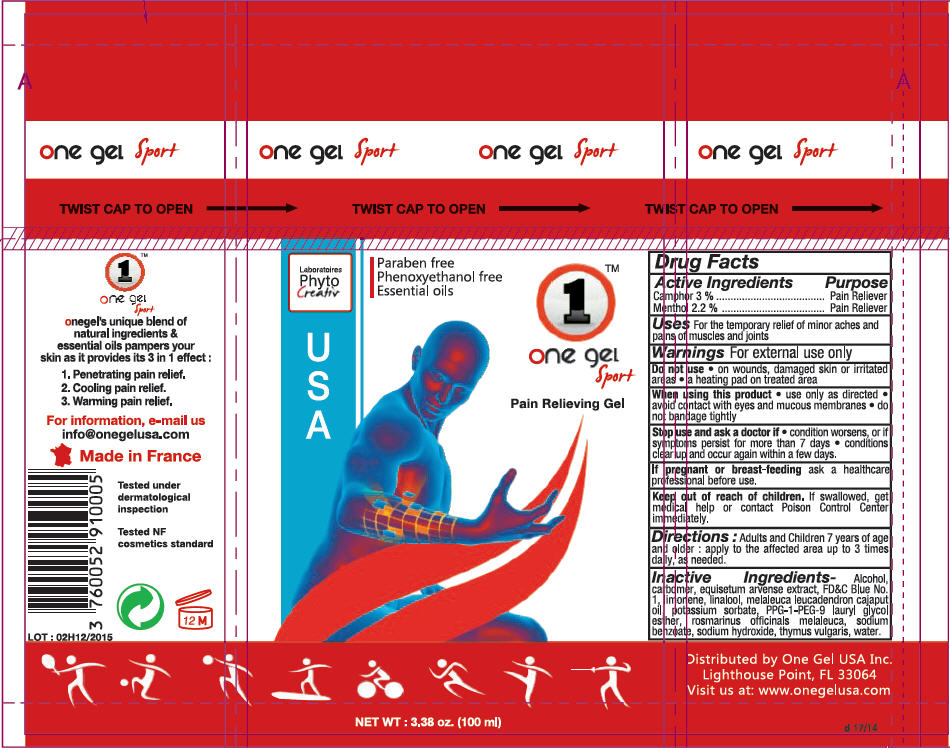 DRUG LABEL: One Gel Sport 
NDC: 69023-100 | Form: GEL
Manufacturer: Phyto Creativ
Category: otc | Type: HUMAN OTC DRUG LABEL
Date: 20140822

ACTIVE INGREDIENTS: Camphor (Synthetic) 30 mg/1 mL; Menthol 22 mg/1 mL
INACTIVE INGREDIENTS: Alcohol; equisetum arvense branch; fd&c blue no. 1; linalool, (+/-)-; potassium sorbate; sodium benzoate; sodium hydroxide; water

One Gel Sport
Pain relieving gel

Phyto Creativ Drug Facts

ACTIVE INGREDIENT

Active Ingredients | Purpose
Camphor 3% | Pain Reliever
Menthol 2.2% | Pain Reliever

Uses

For the temporary relief of minor aches and pains of muscles and joints

Warnings

For external use only

Do not use on wounds, damaged skin or irritated areas a heating pad on treated area

When using this product use only as directed avoid contact with eyes and mucous membranes do not bandage tightly

Stop use and ask doctor if condition worsens, or if symptoms persist for more than 7 days conditions clear up and occur again within a few days.

PREGNANCY OR BREAST FEEDING

If pregnant or breast-feeding ask a healthcare professional before use.

Keep out of reach of children. If swallowed, get medical help or contact Poison Control Center immediately.

Directions

Adults and Children 7 years of age and older: apply to the affected area up to 3 times daily, as needed.

Inactive Ingredients

Alcohol, carbomer, equisetum arvense extract, FD&C Blue No. 1, limonene, linalool, malaleuca leucadendron cajaput oil, potassium sorbate, PPG-1-PEG-9 lauryl glycol esther, rosmarinus officinals malaleuca, sodium benzoate, sodium hydroxide, thymus vulgaris, water.

Distributed by One Gel USA Inc.
Lighthouse Point, FL 33064

PRINCIPAL DISPLAY PANEL - 100 ml Bottle Label

one gel Sport

TWIST CAP TO OPEN

Laboratoires
Phyto
Creativ

USA

Paraben free
Phenoxyethanol free
Essential oils

①™
one gel
Sport

Pain Relieving Gel

NET WT : 3.38 oz. (100 ml)